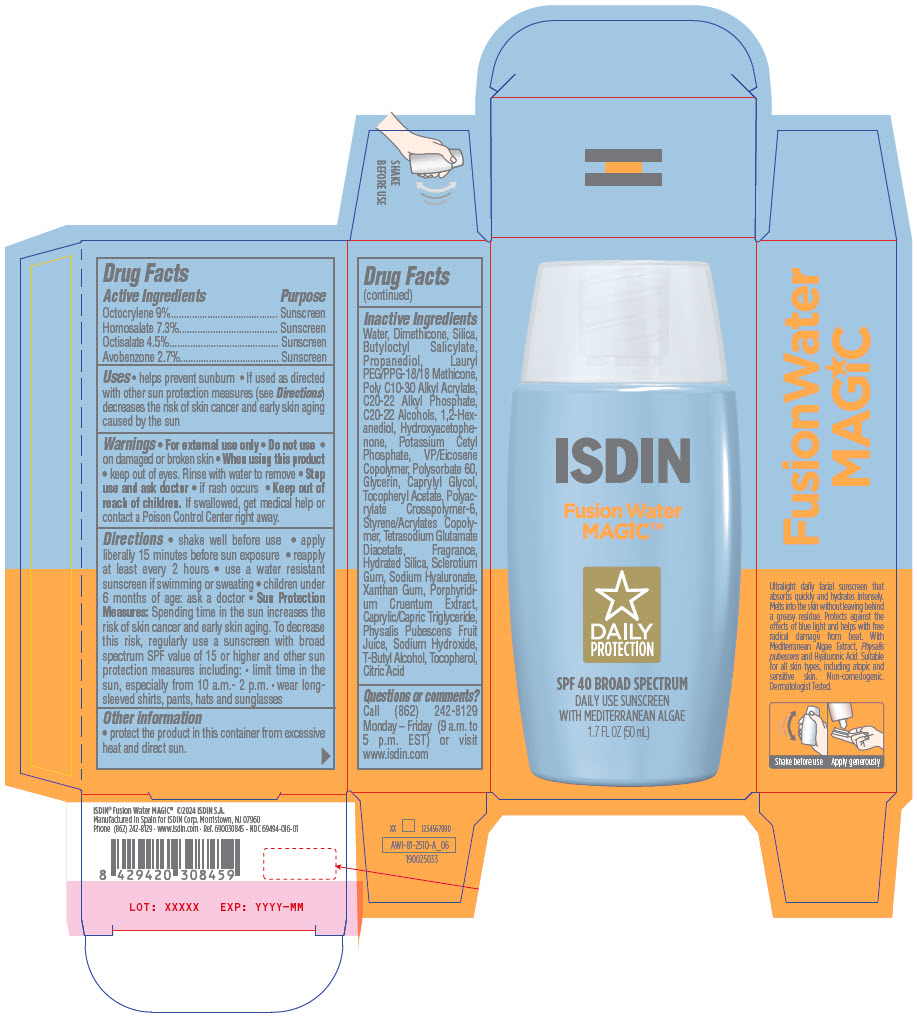 DRUG LABEL: Fusion Water Magic
NDC: 69494-016 | Form: LOTION
Manufacturer: ISDIN Corp.
Category: otc | Type: HUMAN OTC DRUG LABEL
Date: 20250821

ACTIVE INGREDIENTS: Octocrylene 90 mg/1 mL; Homosalate 73 mg/1 mL; Octisalate 45 mg/1 mL; Avobenzone 27 mg/1 mL
INACTIVE INGREDIENTS: Butyloctyl Salicylate; Lauryl PEG/PPG-18/18 Methicone; ANHYDROUS CITRIC ACID; XANTHAN GUM; PORPHYRIDIUM PURPUREUM; Sodium Hydroxide; Polysorbate 60; Water; HYALURONATE SODIUM; BETASIZOFIRAN; SILICON DIOXIDE; Glycerin; Dimethicone; BEHENYL ACRYLATE POLYMER; .ALPHA.-TOCOPHEROL ACETATE; Caprylyl Glycol; TERT-BUTYL ALCOHOL; Physalis Pubescens Fruit Juice; Propanediol; MEDIUM-CHAIN TRIGLYCERIDES; Tocopherol; Hydrated Silica; C20-22 Alkyl Phosphate; C20-22 Alcohols; 1,2-HEXANEDIOL; Hydroxyacetophenone; AMMONIUM ACRYLOYLDIMETHYLTAURATE, DIMETHYLACRYLAMIDE, LAURYL METHACRYLATE AND LAURETH-4 METHACRYLATE COPOLYMER, TRIMETHYLOLPROPANE TRIACRYLATE CROSSLINKED (45000 MPA.S); VINYLPYRROLIDONE/EICOSENE COPOLYMER; ACRYLIC ACID; TETRASODIUM GLUTAMATE DIACETATE; Potassium Cetyl Phosphate

Fusion Water Magic™

Drug Facts

ACTIVE INGREDIENT

Active Ingredients | Purpose
Octocrylene 9% | Sunscreen
Homosalate 7.3% | Sunscreen
Octisalate 4.5% | Sunscreen
Avobenzone 2.7% | Sunscreen

Uses

- helps prevent sunburn
- If used as directed with other sun protection measures (see Directions) decreases the risk of skin cancer and early skin aging caused by the sun

Warnings

- For external use only

- Do not use
  - on damaged or broken skin

- When using this product
  - keep out of eyes. Rinse with water to remove

- Stop use and ask doctor
  - if rash occurs

- Keep out of reach of children. If swallowed, get medical help or contact a Poison Control Center right away.

Directions

- shake well before use
- apply liberally 15 minutes before sun exposure
- reapply at least every 2 hours
- use a water resistant sunscreen if swimming or sweating
- children under 6 months of age: ask a doctor
- Sun Protection Measures: Spending time in the sun increases the risk of skin cancer and early skin aging. To decrease this risk, regularly use a sunscreen with broad spectrum SPF value of 15 or higher and other sun protection measures including:
  - limit time in the sun, especially from 10 a.m.- 2 p.m.
  - wear long-sleeved shirts, pants, hats and sunglasses

Other information

- protect the product in this container from excessive heat and direct sun.

Inactive Ingredients

Water, Dimethicone, Silica, Butyloctyl Salicylate, Propanediol, Lauryl PEG/PPG-18/18 Methicone, Poly C10-30 Alkyl Acrylate, C20-22 Alkyl Phosphate, C20-22 Alcohols, 1,2-Hexanediol, Hydroxyacetophenone, Potassium Cetyl Phosphate, VP/Eicosene Copolymer, Polysorbate 60, Glycerin, Caprylyl Glycol, Tocopheryl Acetate, Polyacrylate Crosspolymer-6, Styrene/Acrylates Copolymer, Tetrasodium Glutamate Diacetate, Fragrance, Hydrated Silica, Sclerotium Gum, Sodium Hyaluronate, Xanthan Gum, Porphyridium Cruentum Extract, Caprylic/Capric Triglyceride, Physalis Pubescens Fruit Juice, Sodium Hydroxide, T-Butyl Alcohol, Tocopherol, Citric Acid

Questions or comments?

Call (862) 242-8129 Monday – Friday (9 a.m. to 5 p.m. EST) or visit www.isdin.com

PRINCIPAL DISPLAY PANEL - 50 mL Bottle Carton

ISDIN

Fusion Water
MAGIC™

DAILY
PROTECTION

SPF 40 BROAD SPECTRUM
DAILY USE SUNSCREEN
WITH MEDITERRANEAN ALGAE
1.7 FL OZ (50 mL)